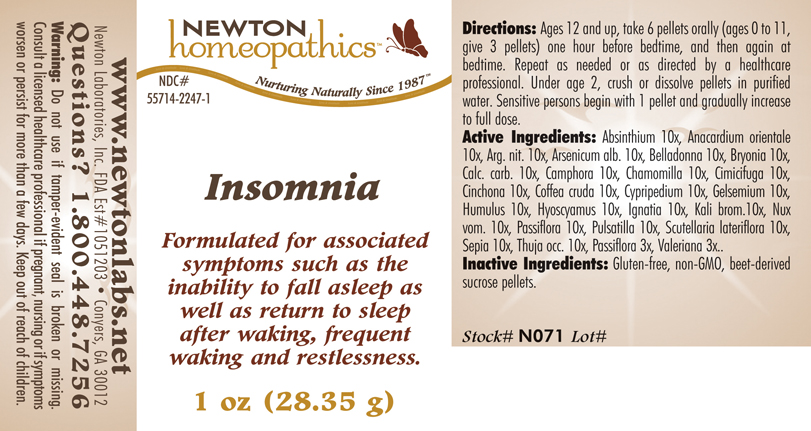 DRUG LABEL: Insomnia 
NDC: 55714-2247 | Form: PELLET
Manufacturer: Newton Laboratories, Inc.
Category: homeopathic | Type: HUMAN OTC DRUG LABEL
Date: 20110301

ACTIVE INGREDIENTS: Wormwood 10 [hp_X]/1 g; Semecarpus Anacardium Juice 10 [hp_X]/1 g; Silver Nitrate 10 [hp_X]/1 g; Arsenic Trioxide 10 [hp_X]/1 g; Atropa Belladonna 10 [hp_X]/1 g; Bryonia Alba Root 10 [hp_X]/1 g; Oyster Shell Calcium Carbonate, Crude 10 [hp_X]/1 g; Camphor (natural) 10 [hp_X]/1 g; Matricaria Recutita 10 [hp_X]/1 g; Black Cohosh 10 [hp_X]/1 g; Cinchona Officinalis Bark 10 [hp_X]/1 g; Arabica Coffee Bean 10 [hp_X]/1 g; Cypripedium Parvifolum Root 10 [hp_X]/1 g; Gelsemium Sempervirens Root 10 [hp_X]/1 g; Hops 10 [hp_X]/1 g; Hyoscyamus Niger 10 [hp_X]/1 g; Strychnos Ignatii Seed 10 [hp_X]/1 g; Potassium Bromide 10 [hp_X]/1 g; Strychnos Nux-vomica Seed 10 [hp_X]/1 g; Passiflora Incarnata Flowering Top 10 [hp_X]/1 g; Pulsatilla Vulgaris 10 [hp_X]/1 g; Scutellaria Lateriflora 10 [hp_X]/1 g; Sepia Officinalis Juice 10 [hp_X]/1 g; Thuja Occidentalis Leafy Twig 10 [hp_X]/1 g; Valerian 3 [hp_X]/1 g
INACTIVE INGREDIENTS: Sucrose

Insomnia

INDICATIONS & USAGE SECTION

Insomnia Formulated for associated symptoms such as the inability to fall asleep as well as return to sleep after waking, frequent waking and restlessness.

DOSAGE & ADMINISTRATION SECTION

Directions: Ages 12 and up, take 6 pellets orally (ages 0 to 11, give 3 pellets) one hour before bedtime, and then again at bedtime. Repeat as needed or as directed by a healthcare professional. Under age 2, crush or dissolve pellets in purified water. Sensitive persons begin with 1 pellet and gradually increase to full dose.

OTC - ACTIVE INGREDIENT SECTION

Absinthium 10x, Anacardium orientale 10x, Arg. nit. 10x, Arsenicum alb. 10x, Belladonna 10x, Bryonia 10x, Calc. carb. 10x, Camphora 10x, Chamomilla 10x, Cimicifuga 10x, Cinchona 10x, Coffea cruda 10x, Cypripedium 10x, Gelsemium 10x, Humulus 10x, Hyoscyamus 10x, Ignatia 10x, Kali brom.10x, Nux vom. 10x, Passiflora 10x, Pulsatilla 10x, Scutellaria lateriflora 10x, Sepia 10x, Thuja occ. 10x, Passiflora 3x, Valeriana 3x.

OTC - PURPOSE SECTION

Formulated for associated symptoms such as the inability to fall asleep as well as return to sleep after waking, frequent waking and restlessness.

INACTIVE INGREDIENT SECTION

Inactive Ingredients: Gluten-free, non-GMO, beet-derived sucrose pellets.

QUESTIONS SECTION

www.newtonlabs.net Newton Laboratories, Inc. FDA Est # 1051203 - Conyers, GA 30012
Questions? 1.800.448.7256

WARNINGS SECTION

Warning: Do not use if tamper - evident seal is broken or missing. Consult a licensed healthcare professional if pregnant, nursing or if symptoms worsen or persist for more than a few days. Keep out of reach of children.

OTC - PREGNANCY OR BREAST FEEDING SECTION

Consult a licensed healthcare professional if pregnant, nursing or if symptoms worsen or persist for more than a few days

OTC - KEEP OUT OF REACH OF CHILDREN SECTION

Keep out of reach of children.